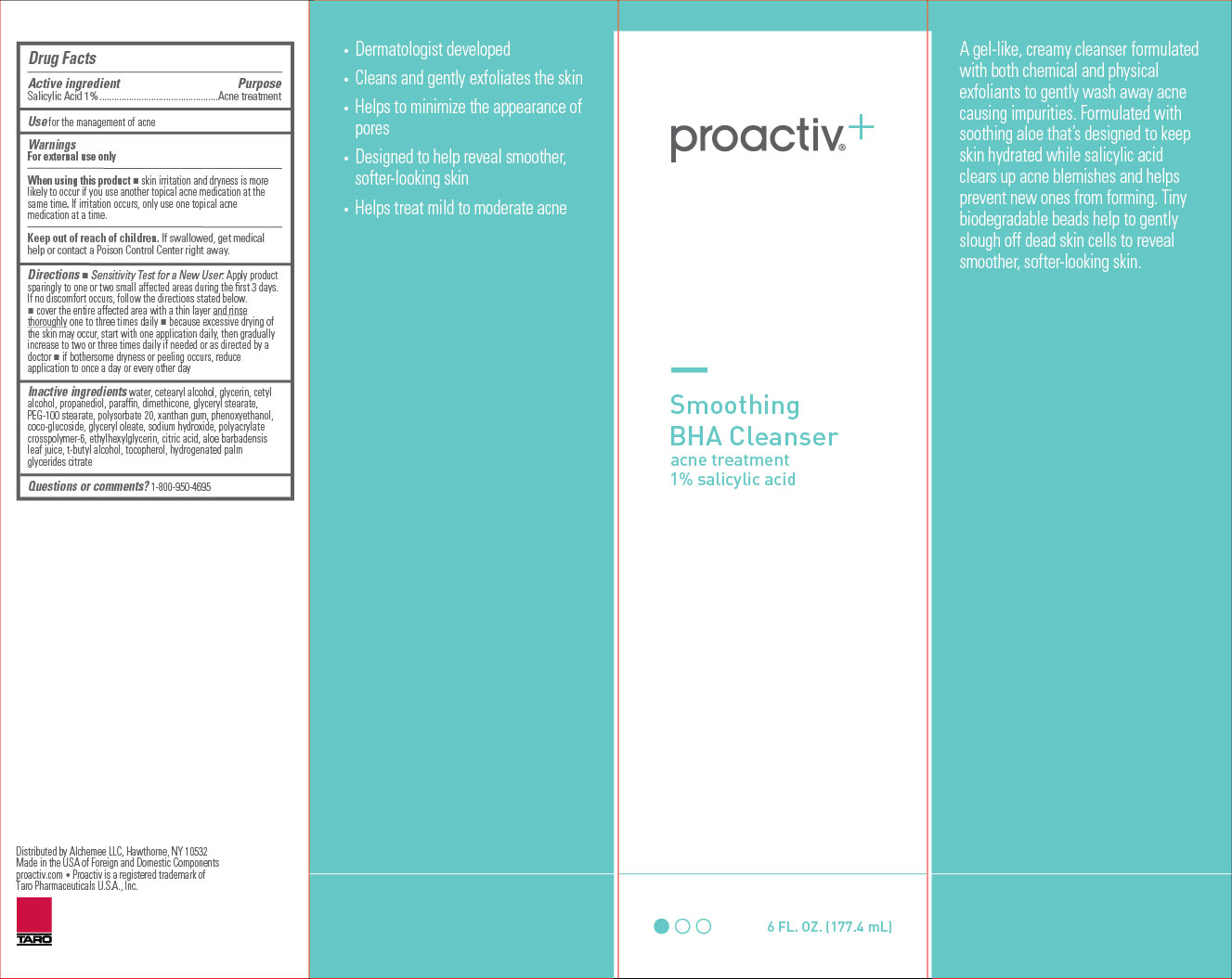 DRUG LABEL: Proactivplus Smoothing BHA Cleanser
NDC: 11410-216 | Form: LIQUID
Manufacturer: Alchemee, LLC
Category: otc | Type: HUMAN OTC DRUG LABEL
Date: 20260107

ACTIVE INGREDIENTS: SALICYLIC ACID 10 mg/1 mL
INACTIVE INGREDIENTS: WATER; GLYCERIN; DIMETHICONE; ETHYLHEXYLGLYCERIN; GLYCOLIC ACID; SODIUM HYDROXIDE; PHENOXYETHANOL; PARAFFIN; GLYCERYL MONOSTEARATE; XANTHAN GUM; HYDROGENATED PALM GLYCERIDES CITRATE; CETOSTEARYL ALCOHOL; PROPANEDIOL; PEG-100 STEARATE; POLYSORBATE 20; COCO-GLUCOSIDE; ALOE VERA LEAF; AMMONIUM ACRYLOYLDIMETHYLTAURATE, DIMETHYLACRYLAMIDE, LAURYL METHACRYLATE AND LAURETH-4 METHACRYLATE COPOLYMER, TRIMETHYLOLPROPANE TRIACRYLATE CROSSLINKED (45000 MPA.S); TERT-BUTYL ALCOHOL; GLYCERYL OLEATE; TOCOPHEROL; CETYL ALCOHOL; CITRIC ACID MONOHYDRATE

Proactiv+ Smoothing BHA Cleanser

Drug Facts

Active ingredient

Salicylic Acid 1%

Purpose

Acne treatment

Use

for the management of acne

Warnings

For external use only

When using this product

- skin irritation and dryness is more likely to occur if you use another topical acne medication at the same time. If irritation occurs, only use one topical acne medication at a time.

Keep out of reach of children.

If swallowed, get medical help or contact a Poison Control Center right away.

Directions

- Sensitivity Test for a New User. Apply product sparingly to one or two small affected areas during the first 3 days. If no discomfort occurs, follow the directions stated below.
- cover the entire affected area with a thin layer and rinse thoroughlyone to three times daily
- because excessive drying of the skin may occur, start with one application daily, then gradually increase to two or three times daily if needed or as directed by a doctor
- if bothersome dryness or peeling occurs, reduce application to once a day or every other day
- if going outside, apply sunscreen after using this product. If irritation or sensitivity develops, stop use of both products and ask a doctor.

Inactive ingredients

Water, Cetearyl Alcohol, Glycerin, Cetyl Alcohol, Propanediol, Paraffin, Dimethicone, Glyceryl Stearate, PEG-100 Stearate, Polysorbate 20, Xanthan Gum, Phenoxyethanol, Coco-Glucoside, Glyceryl Oleate, Sodium Hydroxide, Polyacrylate Crosspolymer-6, Ethylhexylglycerin, Citric Acid, Aloe Barbadensis Leaf Juice, t-Butyl Alcohol, Tocopherol, Hydrogenated Palm Glycerides Citrate.

Questions or comments?

1-800-950-4695

Distributed by Alchemee LLC, Hawthorne, NY 10532
Made in the USA of Foreign and Domestic Components
Questions? 1-800-950-4695 • proactiv.com • Proactiv is a
registered trademark of Taro Pharmaceuticals U.S.A., Inc.

PRINCIPAL DISPLAY PANEL - 60 mL Carton

proactiv^+

Smoothing

BHA Cleanser
acne treatment

1% salicylic acid

6 FL. OZ. (177.4 mL)